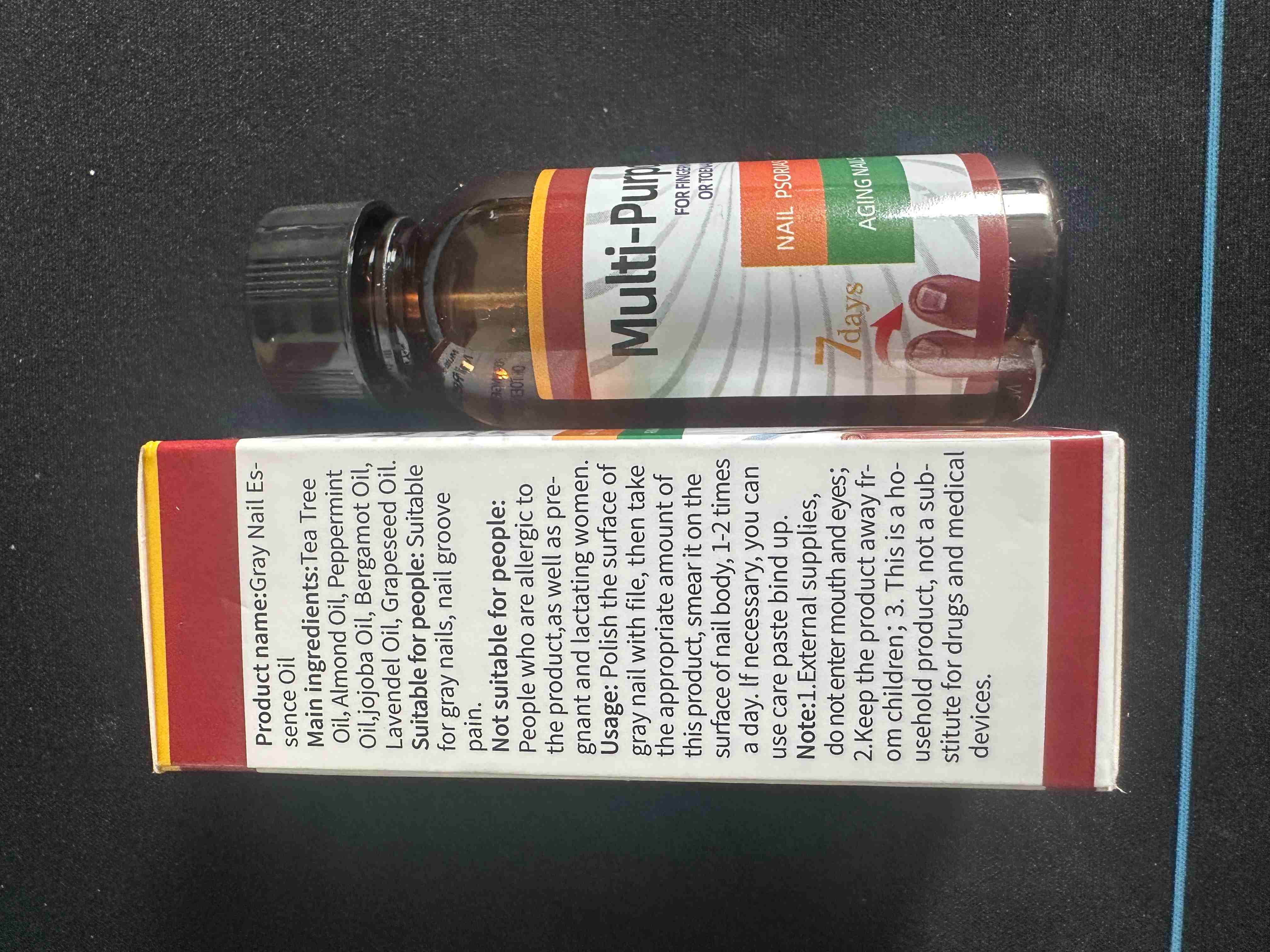 DRUG LABEL: Gray Nail Essence Oil
NDC: 85593-002 | Form: LIQUID
Manufacturer: Guangzhou ChuanMa International Trading Co.,Ltd.
Category: otc | Type: HUMAN OTC DRUG LABEL
Date: 20250715

ACTIVE INGREDIENTS: PEPPERMINT OIL 1 g/100 mL
INACTIVE INGREDIENTS: TEA TREE OIL; JOJOBA OIL; GRAPE SEED OIL; BERGAMOT OIL; ALMOND OIL; LAVENDER OIL

ACTIVE INGREDIENT

Peppermint：1%

INACTIVE INGREDIENT

Camomile Essential Oil

Almond Oil

Jojoba Oil

Bergamot Oil

Lavender Oil

Grape Seed Oil

PURPOSE

Penetates The NailRepair Onychomycosis deeply
Strong FormulaRenew damaged nail faster
Multi-PurposeFor various types of damagednails

INDICATIONS AND USAGE

Usage: Polish the surface ofgray nail with file, then takethe appropriate amount ofthis product, smear it on thesurface of nail body, 1-2 timesa day. lf necessary, you canuse care paste bind up.

DO NOT USE

Not suitable for people:People who are allergic tothe product,as well as pre-gnant and lactating women.

2.Keep the product away from children;

WARNINGS

Note:1.External supplies,do not enter mouth and eyes;2.Keep the product away fr-om children; 3. This is a ho-usehold product, not a sub-stitute for drugs and medicaldevices.

OTHER SAFETY INFORMATION

Suitable for people: Suitablefor gray nails, nail groovepain.Not suitable for people:People who are allergic tothe product,as well as pre-gnant and lactating women.

DOSAGE AND ADMINISTRATION

Usage: Polish the surface ofgray nail with file, then takethe appropriate amount ofthis product, smear it on thesurface of nail body, 1-2 timesa day. lf necessary,you canuse care paste bind up.